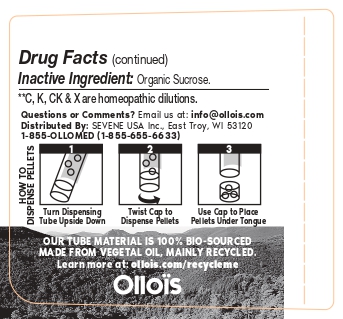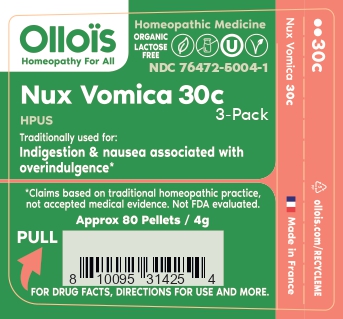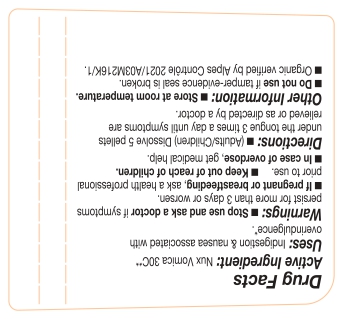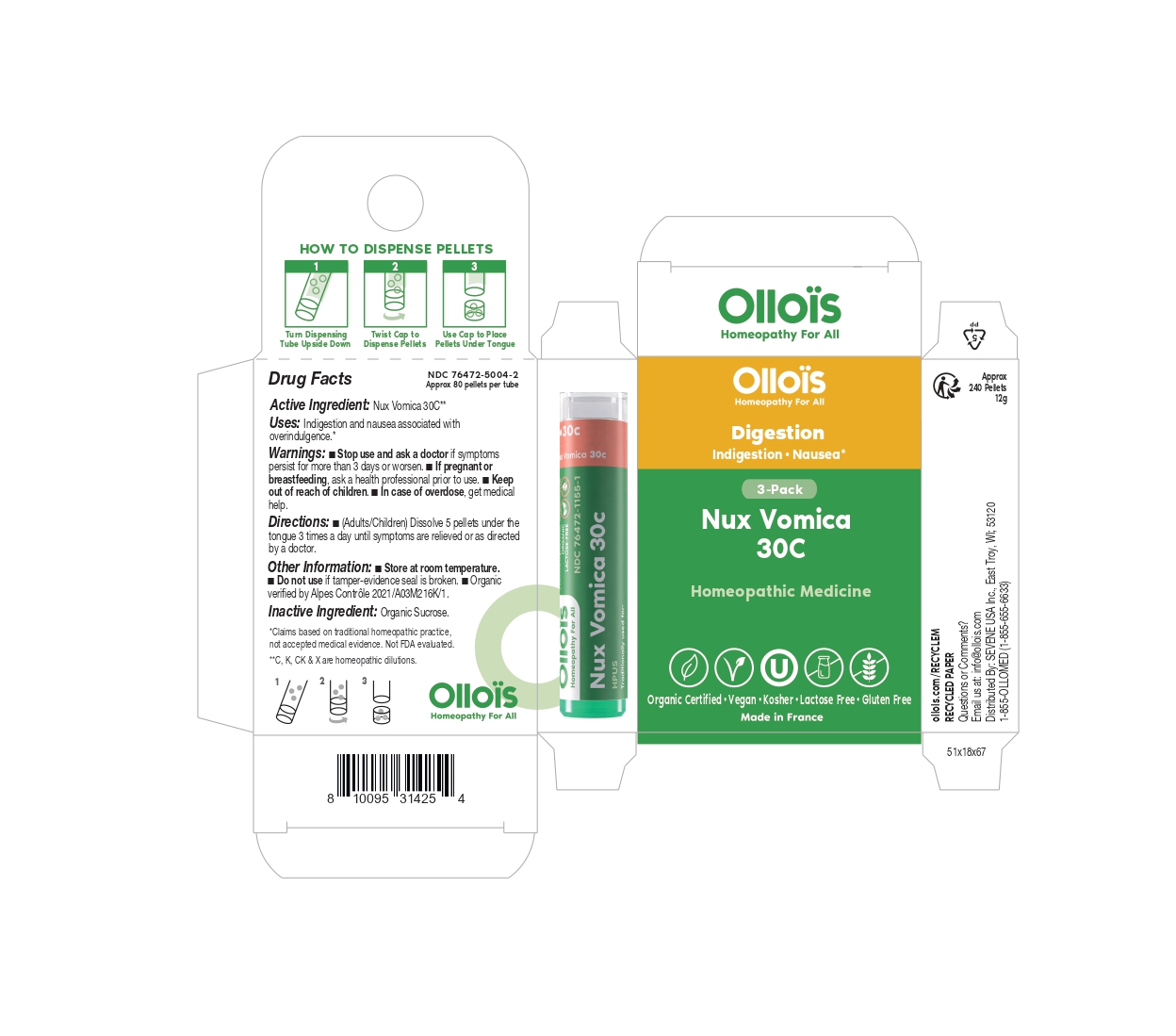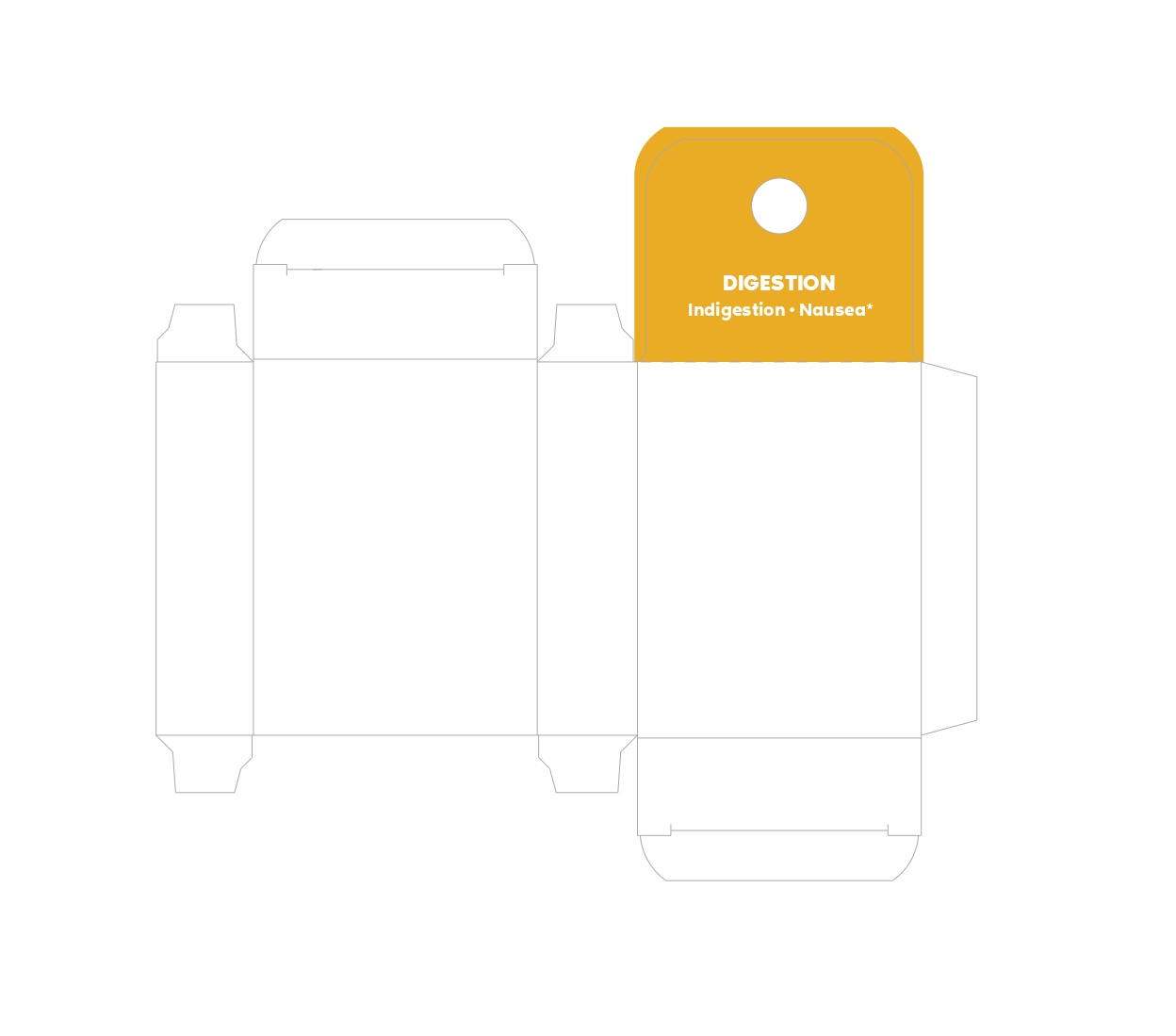 DRUG LABEL: Nux vomica 30C - 3-Pack
NDC: 76472-5004 | Form: PELLET
Manufacturer: SEVENE USA
Category: homeopathic | Type: HUMAN OTC DRUG LABEL
Date: 20250515

ACTIVE INGREDIENTS: STRYCHNOS NUX-VOMICA SEED 30 [hp_C]/1 1
INACTIVE INGREDIENTS: SUCROSE

ACTIVE INGREDIENT

HOMEOPATHIC DILUTION OF NUX VOMICA 30c

TRADITIONALLY USED FOR

Indigestion & nausea associated with overindulgence*

*Claims based on traditional homeopathic practice, not accepted medical evidence. Not FDA evaluated.

DIRECTIONS

(adults/children) Dissolve 5 pellets under the tongue 3 times a day until symptoms are relieved or as directed by a physician.

USE

Condition listed above or as directed by a physician.

WARNINGS

Stop use and ask a physician if symptoms persist for more than 3 days or worsen.

PREGNANCY OR BREAST FEEDING

If pregnant or breast-feeding, ask a health professional before use.

KEEP OUT OF REACH OF CHILDREN

OTHER INFORMATION

Store at room temperature.

Do not use if pellet-dispenser seal is broken.

INACTIVE INGREDIENTS

Sucrose.

QUESTIONS?

info@ollois.com * www.ollois.com * MADE IN FRANCE. NOT REVIEWED BY THE FDA AND NOT GUARANTEED TO BE EFFECTIVE. THIS HOMEOPATHIC DILUTION MAY NOT BE SUSEPTIBLE TO SCIENTIFIC MEASUREMENT.